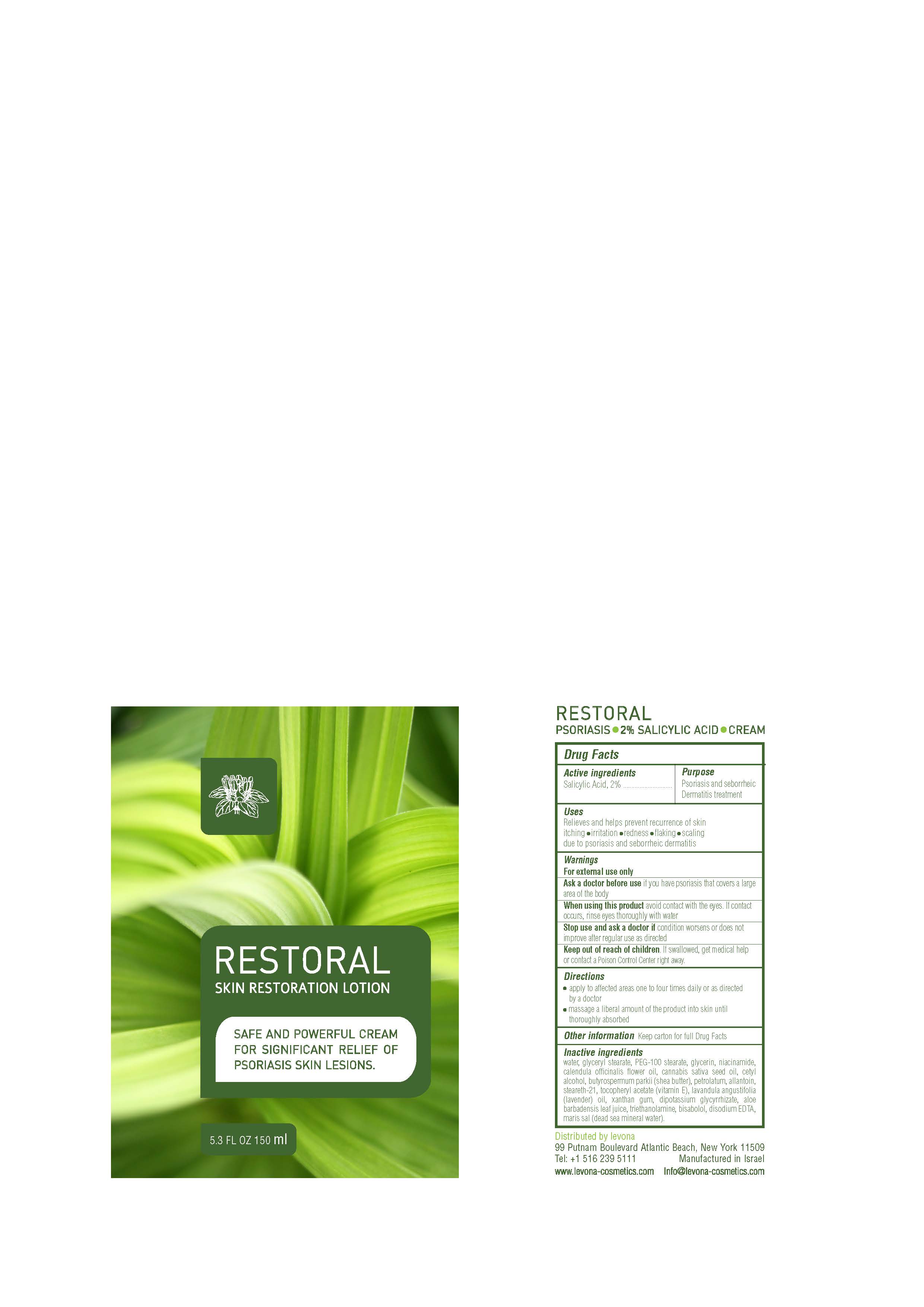 DRUG LABEL: Restoral
NDC: 69435-1805 | Form: CREAM
Manufacturer: Peer Pharma Ltd.
Category: otc | Type: HUMAN OTC DRUG LABEL
Date: 20180614

ACTIVE INGREDIENTS: SALICYLIC ACID 3 g/150 mL
INACTIVE INGREDIENTS: SODIUM CHLORIDE; ALOE VERA LEAF; STEARETH-21; GLYCERYL MONOSTEARATE; WATER; CANNABIS SATIVA SEED OIL; SHEA BUTTER; PETROLATUM; .ALPHA.-TOCOPHEROL ACETATE; LAVENDER OIL; GLYCYRRHIZINATE DIPOTASSIUM; TROLAMINE SALICYLATE; LEVOMENOL; EDETATE DISODIUM ANHYDROUS; CETYL ALCOHOL; CALENDULA OFFICINALIS FLOWER; PEG-100 STEARATE; GLYCERIN; NIACINAMIDE; ALLANTOIN; XANTHAN GUM

Restoral

PACKAGE LABEL

ACTIVE INGREDIENT

Salicylic Acid, 2%

Keep out of reach of children. If swallowed, get medical help or contact a Poison Control Center right away.

Uses
Relieves and helps prevent recurrence of skin itching

- irritation
- redness
- flaking
- scaling

due to psoriasis and seborrheic dermatitis

Directions

- apply to affected areas one to four times daily or as directed by a doctor
- massage a liberal amount of the product into skin until thoroughly absorbed

Directions

- apply to affected areas one to four times daily or as directed by a doctor
- massage a liberal amount of the product into skin until thoroughly absorbed

Inactive ingredients

water, glyceryl stearate, PEG-100 stearate, glycerin, niacinamide, calendula officinalis flower oil, cannabis sativa seed oil, cetyl alcohol, butyrospermum parkii (shea butter), petrolatum, allantoin, steareth-21, tocopheryl acetate (vitamin E), lavandula angustifolia (lavender) oil, xanthan gum, dipotassium glycyrrhizate, aloe barbadensis leaf juice, triethanolamine, bisabolol, disodium EDTA, maris sal (dead sea mineral water).